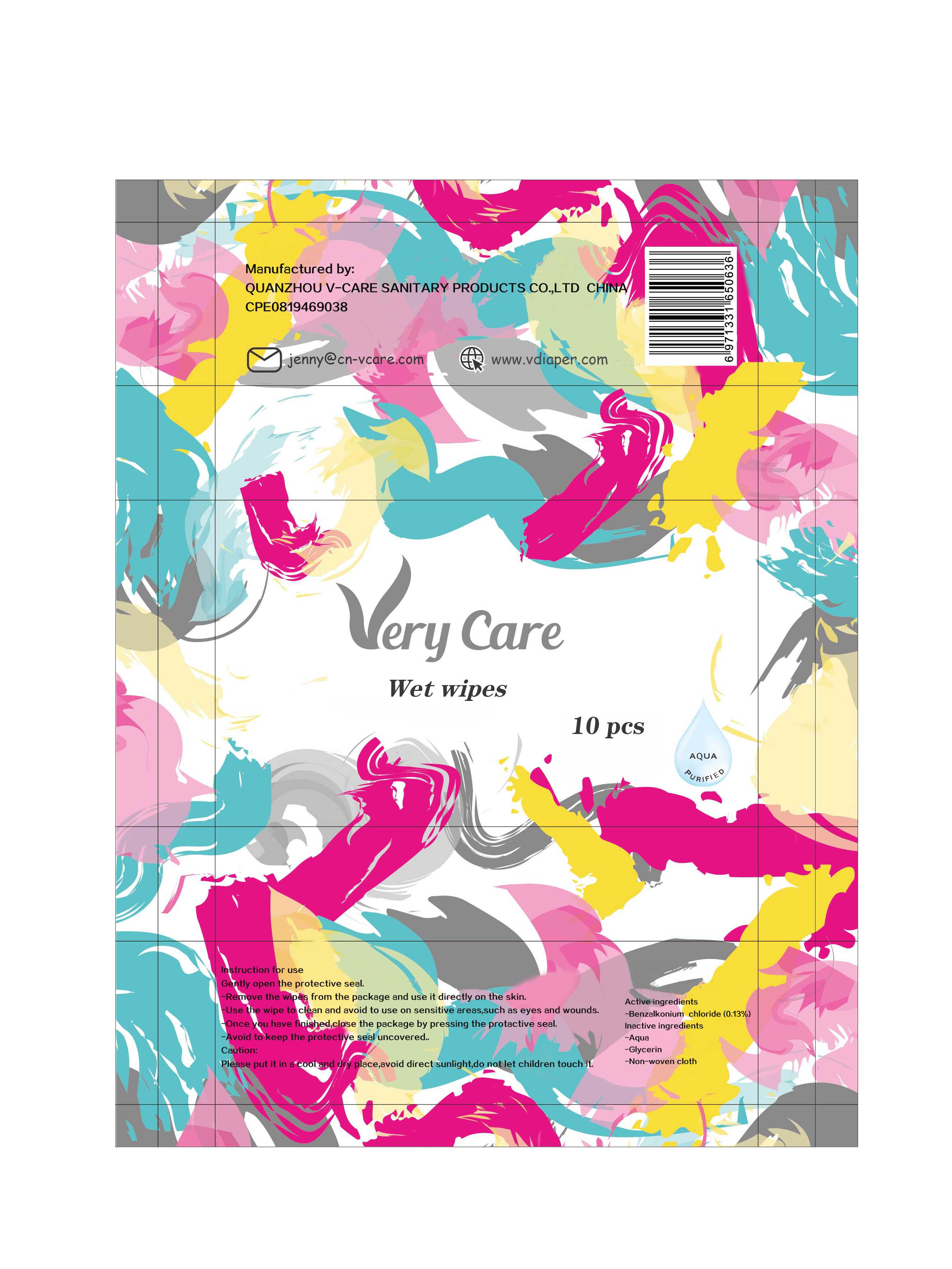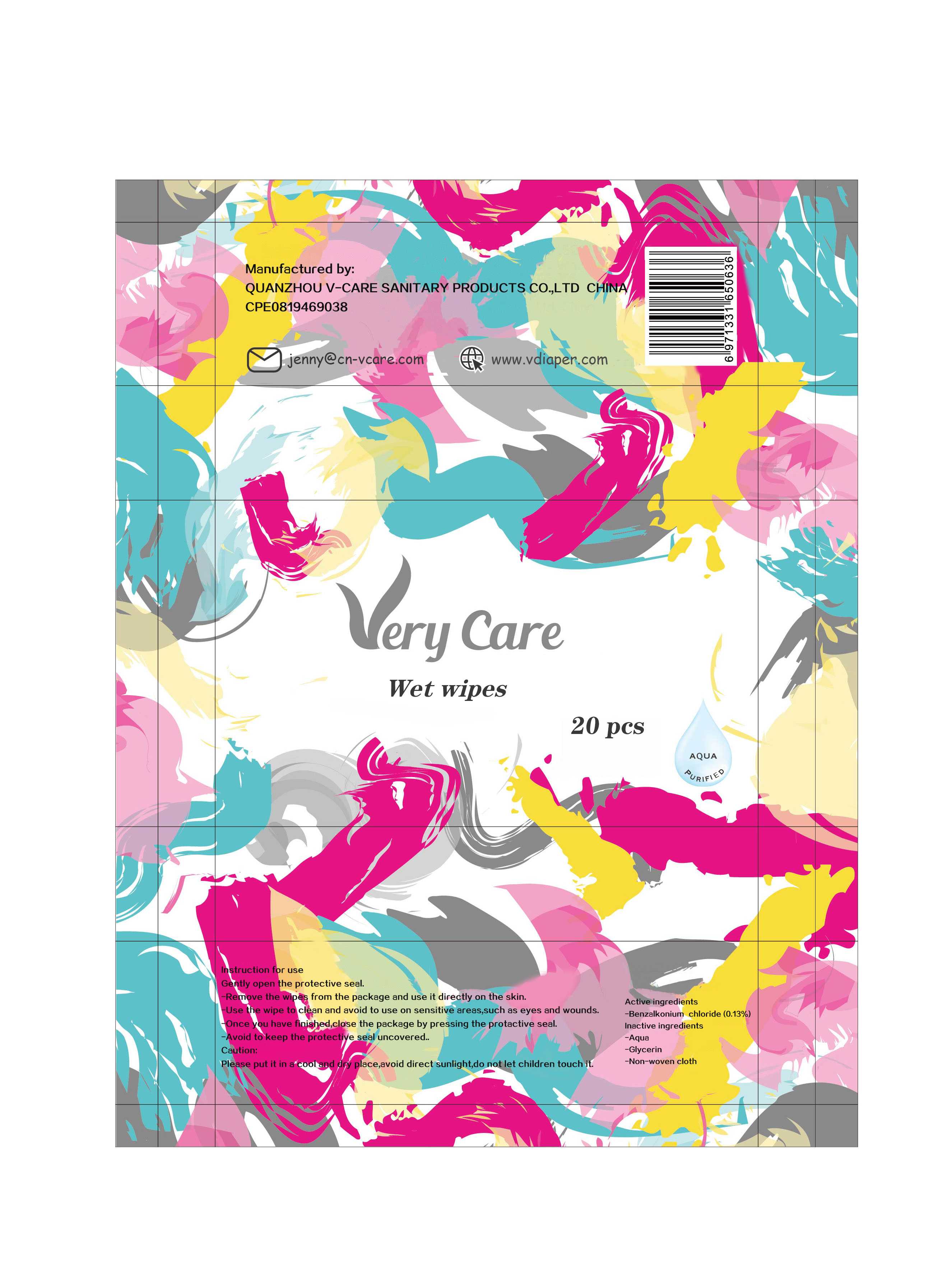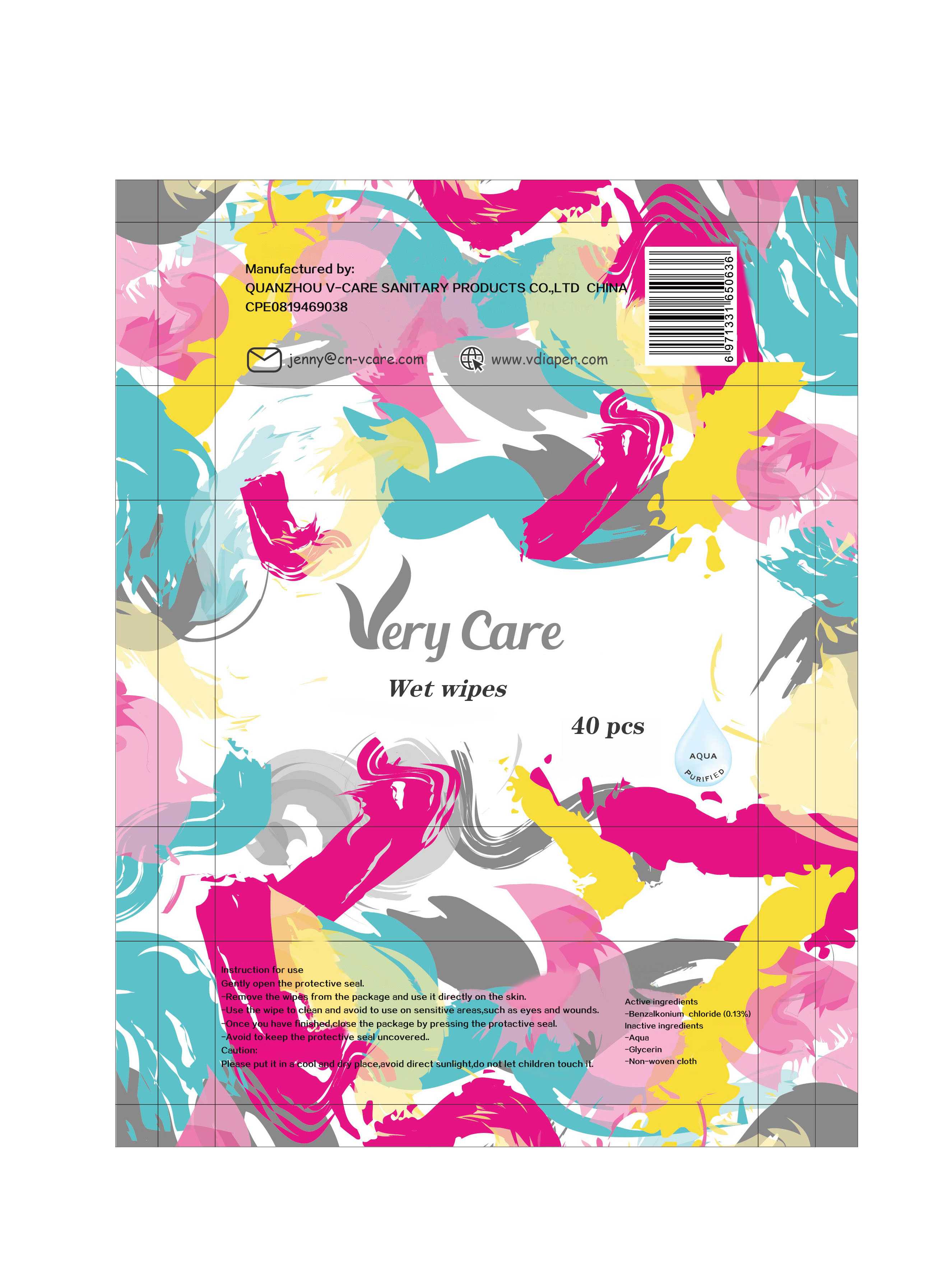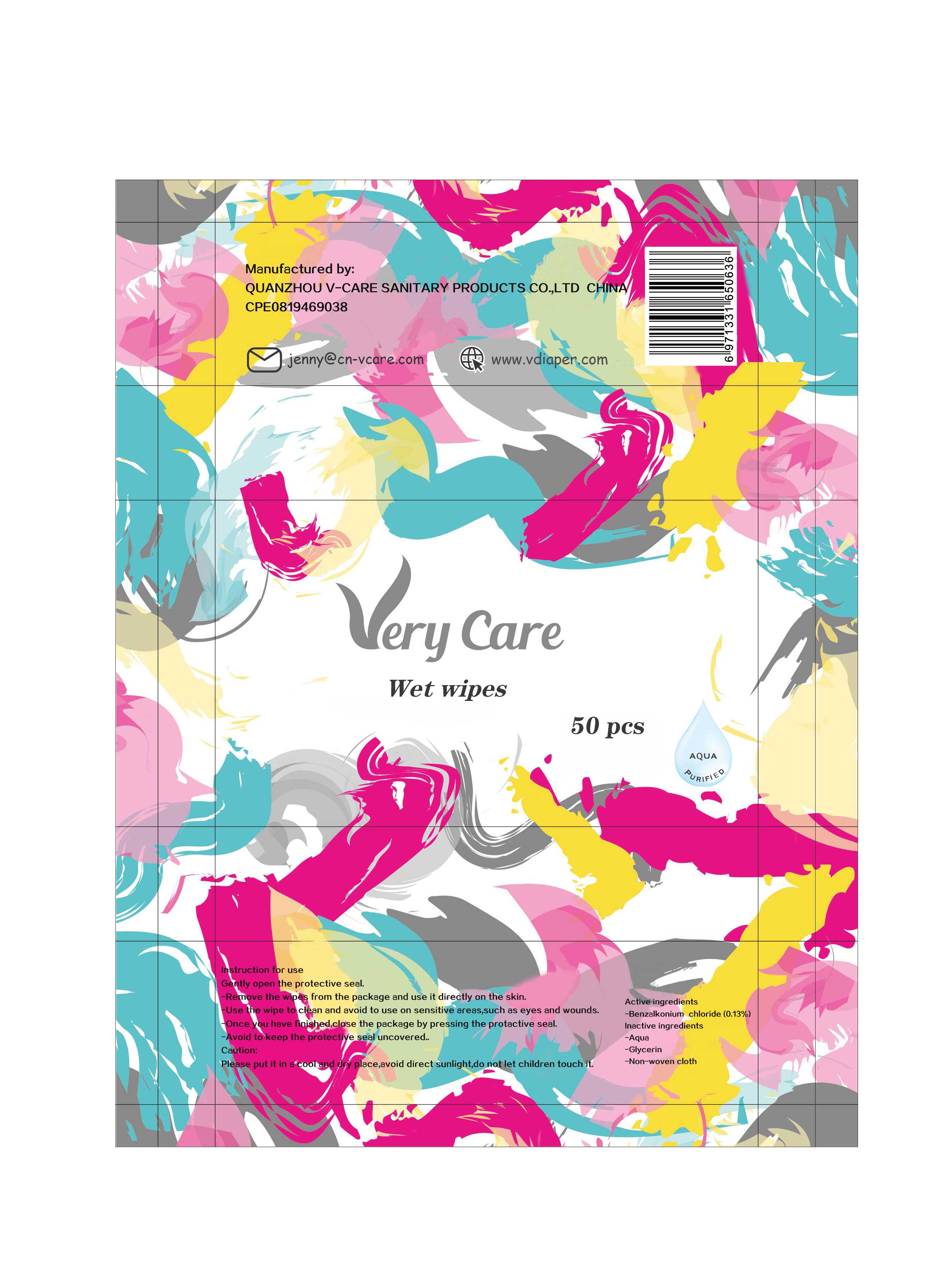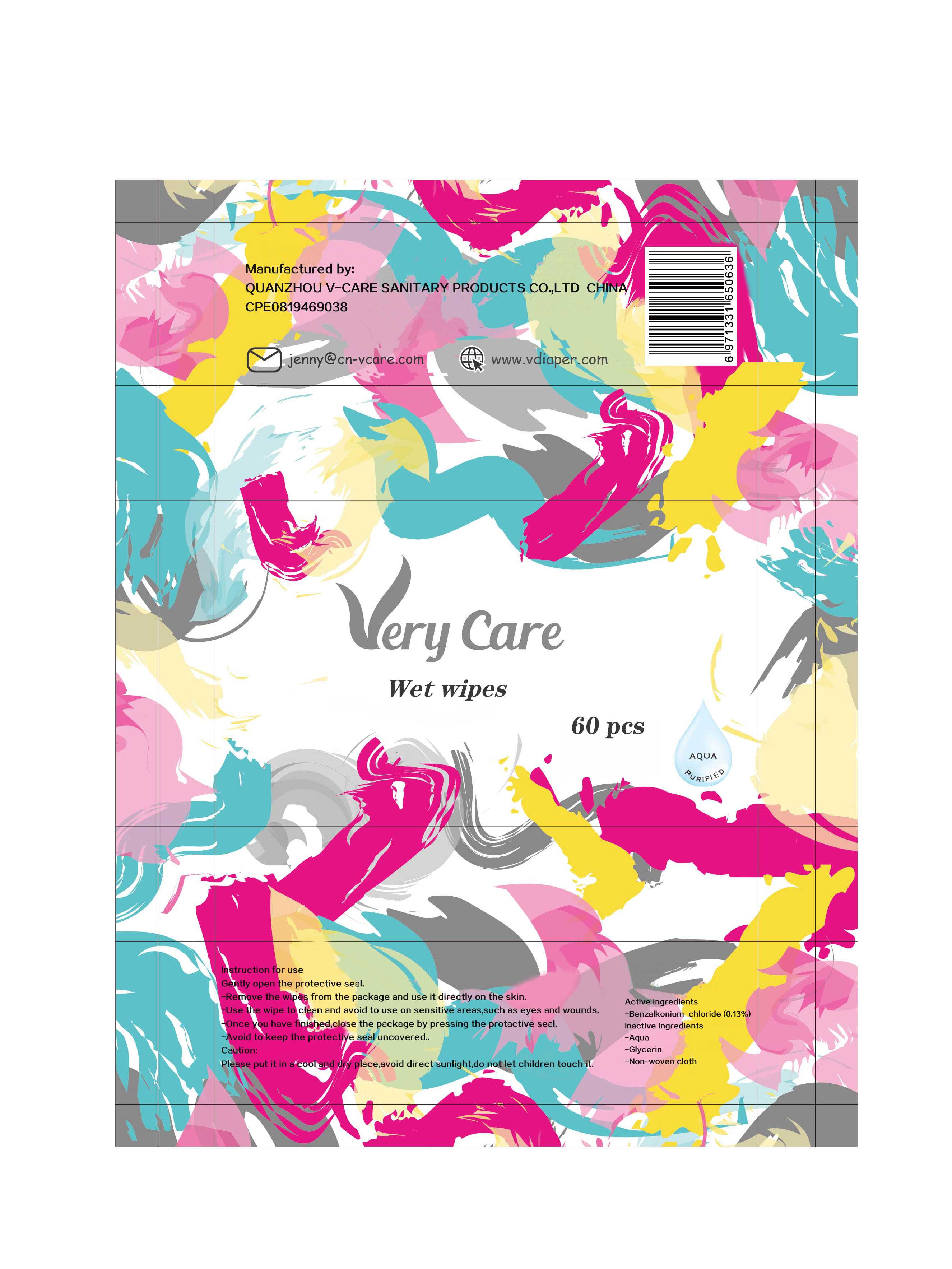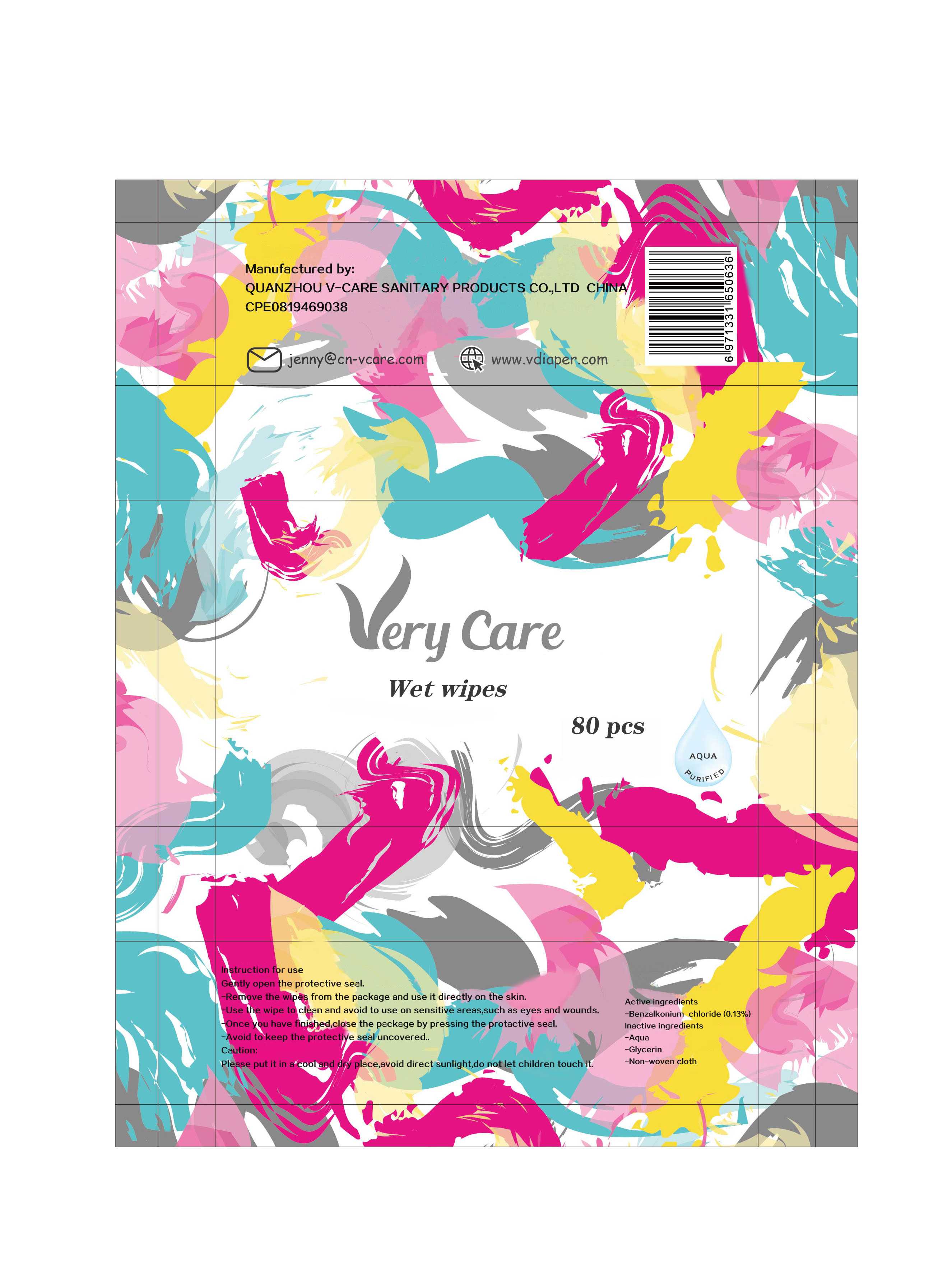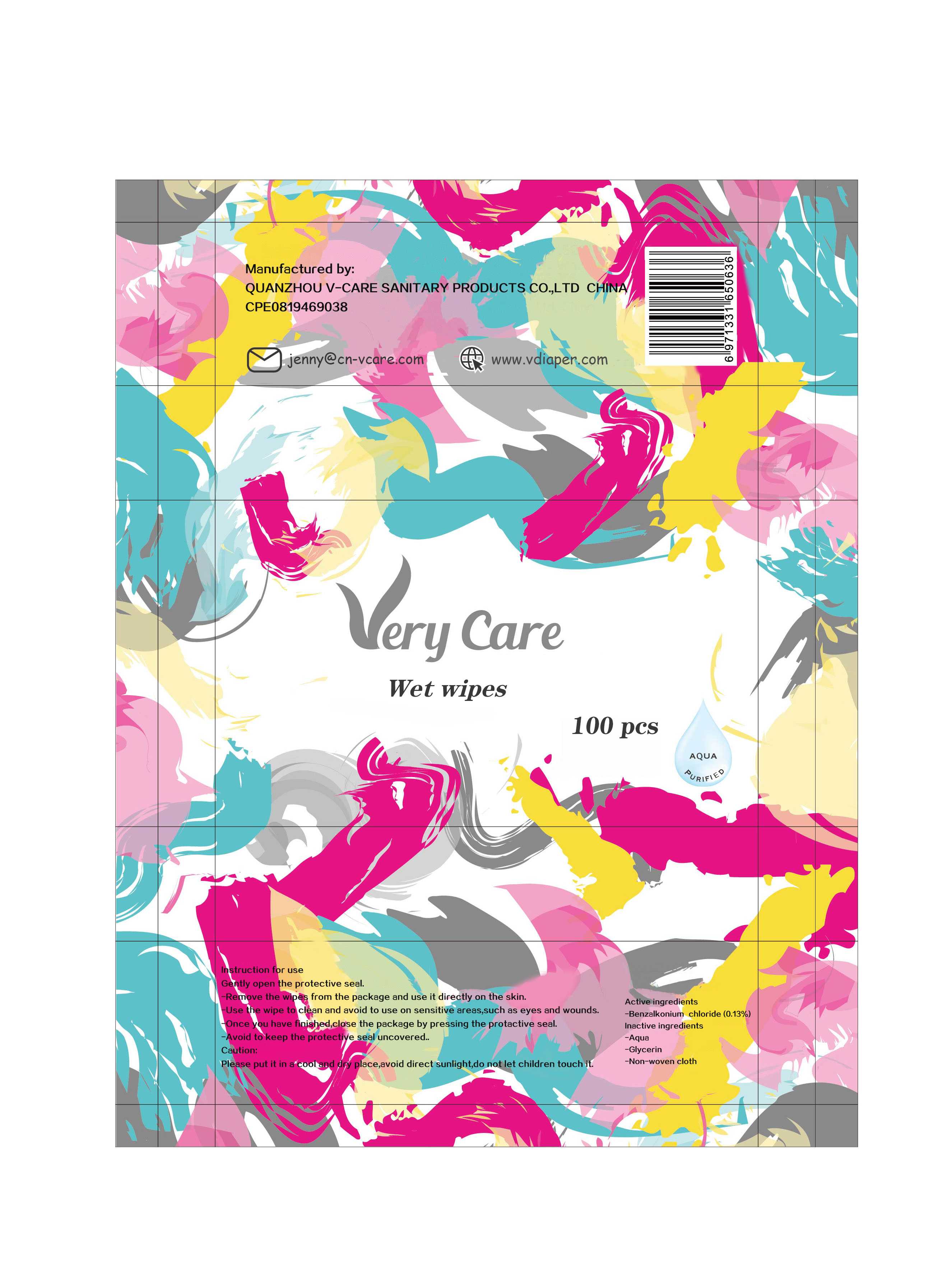 DRUG LABEL: Wet wipes
NDC: 80515-003 | Form: CLOTH
Manufacturer: QUANZHOU V-CARE SANITARY PRODUCTS CO.,LTD
Category: otc | Type: HUMAN OTC DRUG LABEL
Date: 20200904

ACTIVE INGREDIENTS: BENZALKONIUM CHLORIDE 0.13 g/100 1
INACTIVE INGREDIENTS: WATER; GLYCERIN

80515-003
Wet wipes

Active Ingredient(s)

Benzalkonium chloride (0.13%)

Purpose

/

Use

Instruction for use

Warnings

When using this product
Caution:Please put it in a cootapd dry place, avoid direct sunlight, do not let children touch it

Do not use

/

WHEN USING

Caution:Please put it in a cootapd dry place, avoid direct sunlight, do not let children touch it

STOP USE

/

KEEP OUT OF REACH OF CHILDREN

/

Directions

Gently open the protective seal
Remove the wipes from the package and use it directly on the skin
Use the wipe to clean and avoid to use on sensitive areas, such as eyes and wounds
Once you have finished, close the package by pressing the protactive seal
Avoid to keep the protective seal uncovered

Other information

/

Inactive ingredients

Aqua (75%)
Glycerin(0.5%)